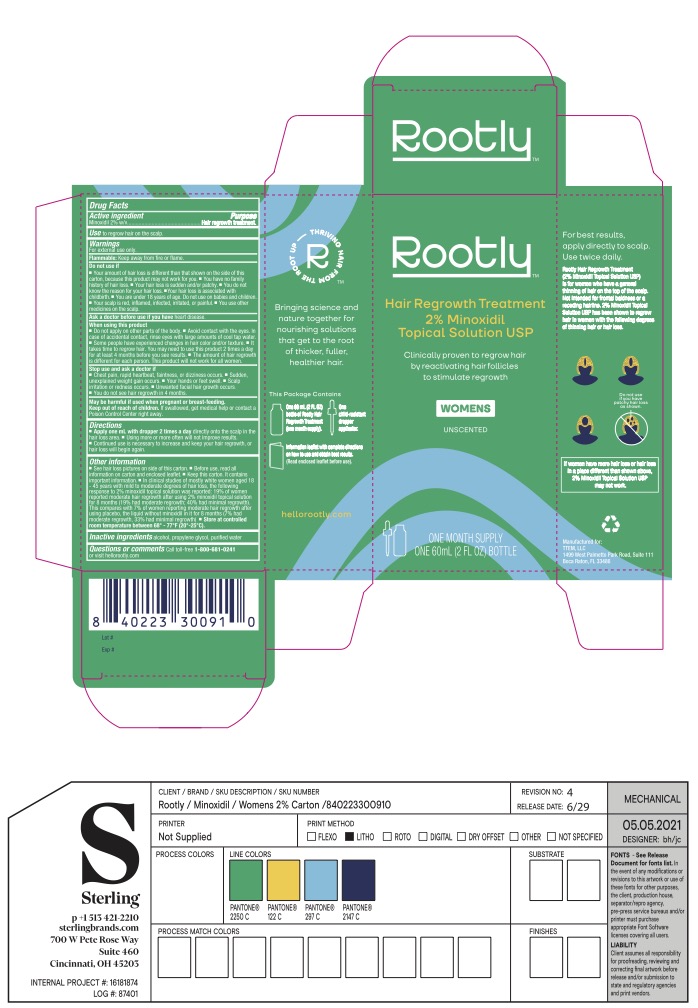 DRUG LABEL: Rootly Hair Regrowth Treatment for Women
NDC: 70150-004 | Form: SOLUTION
Manufacturer: TTEM, LLC
Category: otc | Type: HUMAN OTC DRUG LABEL
Date: 20230118

ACTIVE INGREDIENTS: MINOXIDIL 2 g/100 mL
INACTIVE INGREDIENTS: PROPYLENE GLYCOL; ISOPROPYL ALCOHOL; WATER

Rootly Hair Regrowth Treatment 2% Minoxidil

ACTIVE INGREDIENT

Minoxidil 2% w/v

PURPOSE

Hair regrowth treatment

USE

to regrow hair on scalp

WARNINGS

For external use only

Flammable: Keep away from fire or flame

Do not use if

- Your degree of hair loss is different than that shown on this carton, because this product may not work for you
- You have no family history of hair loss
- Your hair loss is sudden and/or patchy
- Your hair loss is associated with childbirth
- You do not know the reason for your hair loss
- You are under 18 years of age. Do not use on babies or children.
- Your scalp is red, inflammed, infected, irritated, or painful
- You use other medicines on your scalp

Ask a doctor before use if you have heart disease

When using this product

- Do not apply on other parts of the body
- Avoid contact with eyes. In case of accidental contact, rinse eyes with large amounts of cool tap water.
- Some people have experienced change in hair color and/or texture. It takes time to regrow hair. You may need to use this product 2 times a day for at least 4 months before you see results.
- The amount of hair regrow is different for each person. This product will not work for everyone.

Stop use and ask a doctor if

- Chest pain, rapid heartbeat, faintness, or dizziness occurs
- Sudden, unexplained weight gain occurs
- Your hand or feet swell
- Scalp irritation or redness occurs
- Unwanted facial hair growth occurs
- You do not see hair regrowth in 4 months

PREGNANCY OR BREAST FEEDING

May be harmful if used when pregnant or breast-feeding.

KEEP OUT OF REACH OF CHILDREN

If swallowed, get medical help or contact a Poison Control Center right away.

DIRECTIONS

- Apply 1 mL with dropper 2 times a day directly onto the scalp in the hair loss area
- Using more or more often will not improve results
- Continued use is necessary to increase and keep your hair regrowth, or hair loss will begin again

Other Information

- See hair loss pictures on side of this carton
- Before use, read all information on carton and enclosed leaflet
- Keep the carton. It contains important information.
- In clinical studies of mostly white women aged 18-45 years with mild to moderate degrees of hair loss, the following response to 2% minoxidil topical solutions was reported: 19% of women reported moderate hair regrowth after using minoxidil topical solution 2% for 8 months (19% had moderate regrowth: 40% had minimal regrowth). This compares with 7% of women reporting moderate hair regrowth after using the placebo, the liquid without minoxidil in it, for 8 months (7% had moderate regrowth: 33% had minimal regrowth).
- Store at controlled room temperature 68o - 77oF (20o - 25oC).

INACTIVE INGREDIENT

Alcohol, Propylene Glycol, Purified Water

Questions or comments

Call toll-free 1-800-681-0241 or visit hellorootly.com